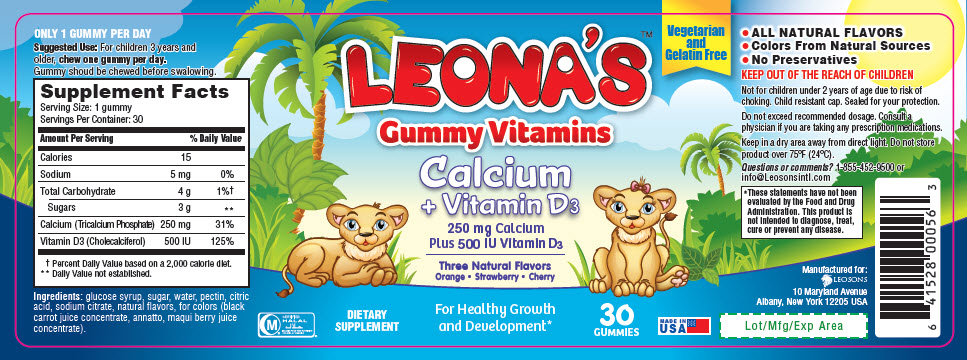 DRUG LABEL: Leonas Calcium Plus Vitamin D3
NDC: 69626-0056 | Form: TABLET, CHEWABLE
Manufacturer: Leosons Overseas Corp
Category: other | Type: DIETARY SUPPLEMENT
Date: 20180920

ACTIVE INGREDIENTS: Calcium 250 mg/1 1; Cholecalciferol 500 [iU]/1 1
INACTIVE INGREDIENTS: Corn Syrup; sucrose; Water; Pectin; Citric Acid Monohydrate; Sodium Citrate, Unspecified Form; Annatto

LEONA'S™ Gummy Vitamins Calcium + Vitamin D3

DOSAGE AND ADMINISTRATION

ONLY 1 GUMMY PER DAY

Suggested Use: For children 3 years and older, chew one gummy per day.

Gummy shoud be chewed before swalowing.

STATEMENT OF IDENTITY

SUPPLEMENT FACTS
Serving Size: 1 gummy
Servings Per Container: 30
Amount Per Serving | %Daily Value
Calories | 15
Sodium | 5 mg | 0%
Total Carbohydrate | 4 g | 1% [Percent Daily Value based on a 2,000 calorie diet]
Sugars | 3 g | [Daily Value not established]
Calcium (Tricalcium Phosphate) | 250 mg | 31%
Vitamin D3 (Cholecalciferol) | 500 IU | 125%

Ingredients: glucose syrup, sugar, water, pectin, citric acid, sodium citrate, natural flavors, for colors (black carrot juice concentrate, annatto, maqui berry juice concentrate).

HEALTH CLAIM

- ALL NATURAL FLAVORS
- Colors From Natural Sources
- No Preservatives

WARNINGS

KEEP OUT OF THE REACH OF CHILDREN

Not for children under 2 years of age due to risk of choking. Child resistant cap. Sealed for your protection.

Do not exceed recommended dosage. Consult a physician if you are taking any prescription medications.

HEALTH CLAIM

Keep in a dry area away from direct light. Do not store product over 75°F (24°C).

Questions or comments? 1-855-452-9500 or info@Leosonsintl.com

HEALTH CLAIM

*These statements have not been evaluated by the Food and Drug Administration. This product is not intended to diagnose, treat, cure or prevent any disease.

HEALTH CLAIM

CERTIFIED
HALAL
ISLAMIC FOOD AND NUTRITION
COUNCIL OF AMERICA

HEALTH CLAIM

Manufactured for:
LEOSONS
10 Maryland Avenue
Albany, New York 12205 USA

HEALTH CLAIM

Lot/Mfg/Exp Area

PRINCIPAL DISPLAY PANEL - 30 Vitamin Bottle Label

Vegetarian
and
Gelatin Free

LEONA'S™
Gummy Vitamins
Calcium
+ Vitamin D3
250 mg Calcium
Plus 500 IU Vitamin D3

Three Natural Flavors
Orange • Strawberry • Cherry

DIETARY
SUPPLEMENT

For Healthy Growth
and Development*

30
GUMMIES

MADE IN
USA